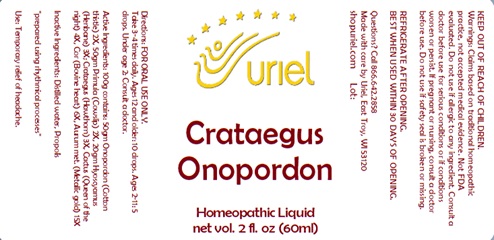 DRUG LABEL: Crataegus Onopordon
NDC: 48951-3136 | Form: LIQUID
Manufacturer: Uriel Pharmacy Inc.
Category: homeopathic | Type: HUMAN OTC DRUG LABEL
Date: 20240306

ACTIVE INGREDIENTS: HAWTHORN LEAF WITH FLOWER 3 [hp_X]/1 mL; SELENICEREUS GRANDIFLORUS STEM 4 [hp_X]/1 mL; BEEF HEART 6 [hp_X]/1 mL; GOLD 15 [hp_X]/1 mL; ONOPORDUM ACANTHIUM FLOWER 2 [hp_X]/1 mL; PRIMULA VERIS FLOWER 2 [hp_X]/1 mL; HYOSCYAMUS NIGER LEAF 3 [hp_X]/1 mL
INACTIVE INGREDIENTS: WATER; PROPOLIS WAX

Crataegus Onopordon

INDICATIONS AND USAGE

Directions: FOR ORAL USE ONLY.

DOSAGE AND ADMINISTRATION

Take 3-4 times daily. Ages 12 and older: 10 drops. Ages 2-11: 5 drops. Under age 2: Consult a doctor.

ACTIVE INGREDIENT

Active Ingredients: 100g contains: 50g Onopordon (Cotton thistle) 2X, 50g Primula (Cowslip) 2X, 20g Hyoscyamus (Henbane) 3X; Crataegus (Hawthorn) 3X, Cactus (Queen of the night) 4X, Cor (Bovine heart) 6X, Aurum met. (Metallic gold) 15X

Inactive Ingredients: Distilled water, Propolis

"prepared using rhythmical processes"

PURPOSE

Use: Temporary relief of headache.

KEEP OUT OF REACH OF CHILDREN.

WARNINGS

Warnings: Claims based on traditional homeopathic practice, not accepted medical evidence. Not FDA evaluated. Do not use if allergic to any ingredient. Consult a doctor before use for serious conditions or if conditions worsen or persist. If pregnant or nursing, consult a doctor before use. Do not use if safety seal is broken or missing.

REFRIGERATE AFTER OPENING.
BEST WHEN USED WITHIN 30 DAYS OF OPENING.

Questions? Call 866.642.2858
Made with care by Uriel, East Troy, WI 53120
shopuriel.com Lot: